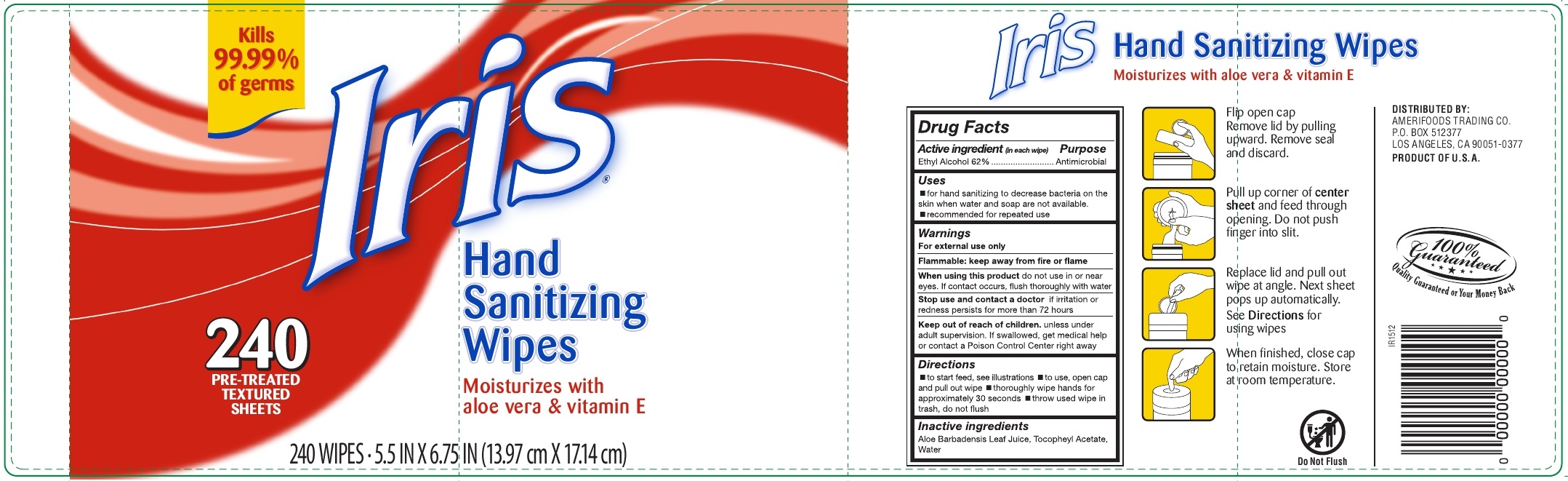 DRUG LABEL: Iris Hand Sanitizing Wipes
NDC: 61504-140 | Form: CLOTH
Manufacturer: Amerifoods Trading Company
Category: otc | Type: HUMAN OTC DRUG LABEL
Date: 20160106

ACTIVE INGREDIENTS: ALCOHOL 62 g/100 g; ALOE VERA LEAF .01 g/100 g; ALPHA-TOCOPHEROL ACETATE .01 g/100 g
INACTIVE INGREDIENTS: WATER 37.98 g/100 g

Active Ingredient (in each wipe)

Ethyl Alcohol .....62%

Purpose

Antimicrobial

Indications and Usages

- For hand sanitizing to decrease bacteria on the skin when water and soap are not available.
- Reccomended for repeated use

Warnings

For external use only

Flammable: keep away from fire or flame

When using this product do not use in or near eyes. If contact occurs, flush thoroughly with water.

Stop use and contact a doctor if irritation or redness persists for more than 72 hours.

Keep out of reach of children unless inder adult supervision. if swallowed, get medical help or contact a Poison Control Center right away.

Keep out of reach of children unless inder adult supervision. if swallowed, get medical help or contact a Poison Control Center right away.

Directions

- To start feed see illustrations
- to use open cap and pull out wipe
- Thoroughly wipe hand for approximately 30 seconds
- throw used wipe in trash
- do not flush

Inactive Ingredients

Aloe barbadensis leaf juice, tocopheryl acetate, water

Label

Kills 99.99% of germs

Iris Hand Sanitizing Wipes

Moisturizes with aloe vera & vitamin E

240 Pre-treated textured sheets

240 wipes 5.5 in x 6.75 in (13.97 cmx 17.14 cm)